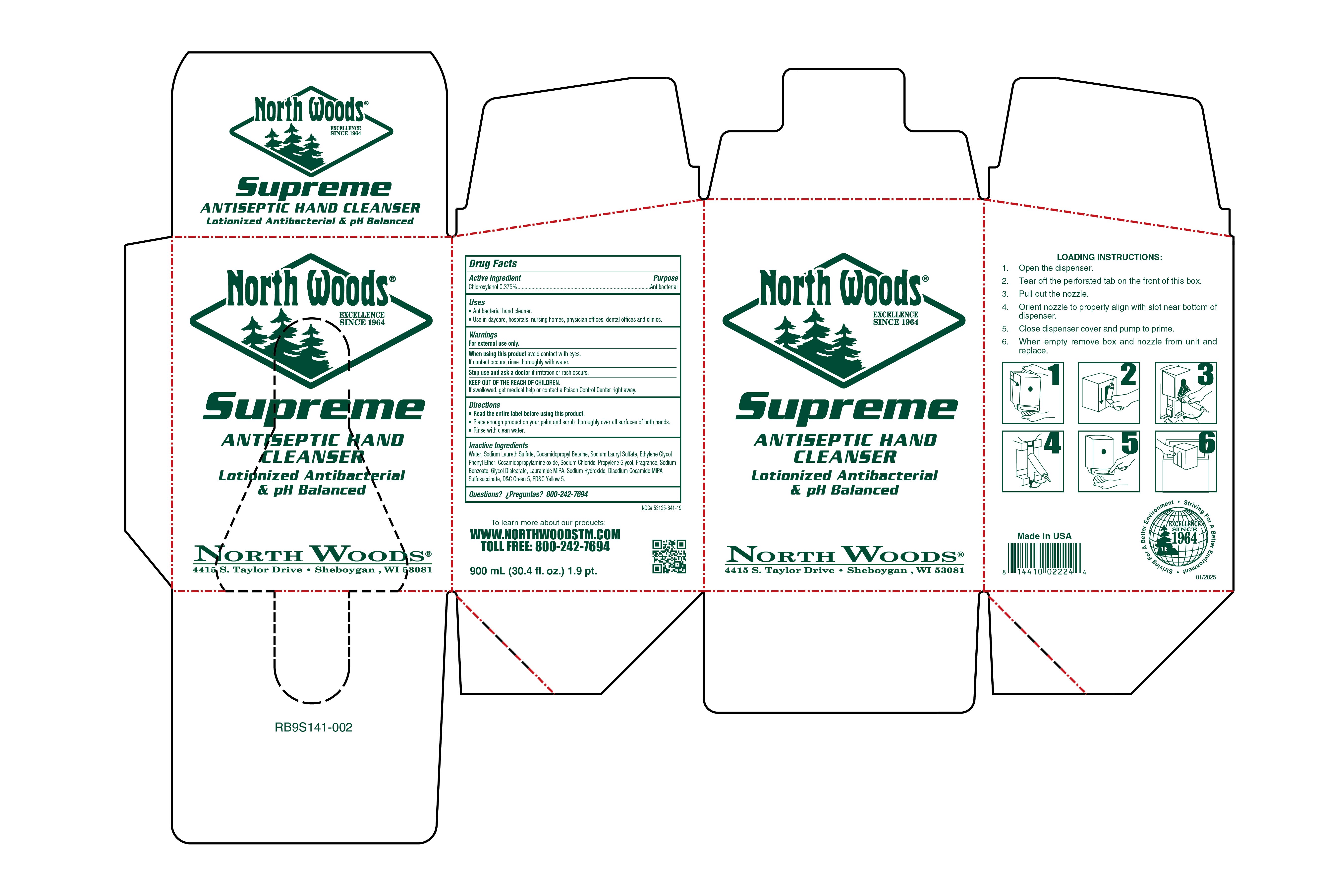 DRUG LABEL: North Woods Supreme Antiseptic Hand Cleaner
NDC: 53125-841 | Form: LIQUID
Manufacturer: Superior Chemical DBA North Woods
Category: otc | Type: HUMAN OTC DRUG LABEL
Date: 20250303

ACTIVE INGREDIENTS: CHLOROXYLENOL 0.375 g/100 mL
INACTIVE INGREDIENTS: BENZYL SALICYLATE; PROPYLENE GLYCOL; DIHYDROMYRCENOL; SODIUM HYDROXIDE; COCAMIDOPROPYLAMINE OXIDE; TRIBASIC CALCIUM PHOSPHATE; 4-ACETOXY-3-PENTYLTETRAHYDROPYRAN; 1-(2,3,8,8-TETRAMETHYL-1,2,3,4,5,6,7,8-OCTAHYDRONAPHTHALEN-2-YL)ETHANONE; PHENYLETHYL ALCOHOL; 2,6-DIMETHYL-5-HEPTENAL; .BETA.-CITRONELLOL, (+/-)-; .GAMMA.-UNDECALACTONE; 2-ISOBUTYL-4-METHYLTETRAHYDROPYRAN-4-OL; ETHYLENE BRASSYLATE; SODIUM CHLORIDE; D&C GREEN NO. 5; FD&C YELLOW NO. 5; SODIUM ALUMINIUM SILICATE; LINALOOL; HEXAHYDRO-4,7-METHANOINDEN-6-YL PROPIONATE; SODIUM LAURYL SULFATE; .ALPHA.-HEXYLCINNAMALDEHYDE; HEXYL SALICYLATE; SODIUM LAURETH SULFATE; COCAMIDOPROPYL BETAINE; .ALPHA.-AMYLCINNAMALDEHYDE; LAURAMIDE MIPA; SODIUM CARBONATE; CALCIUM SILICATE; ETHYLENE OXIDE; GLYCOL DISTEARATE; WATER; 3-(3,4-METHYLENEDIOXYPHENYL)-2-METHYLPROPANAL; 2-TERT-BUTYLCYCLOHEXYL ACETATE; BENZYL ACETATE; SODIUM BENZOATE; PHENOXYETHANOL; VERDYL ACETATE

North Woods Supreme Antiseptic Hand Cleaner

dosage

Place enoiugh product on your palm and scrub thoroughly over all surfaces of both hands

inactive ingredients

Water, Sodium Laureth Sulfate, Cocamidopropyl Betaine, Sodium Lauryl Sulfate, Ethylene Glycol Phenyl Ether, Cocamidopropylamine Oxide, Sodium Chloride, Propylene Glycol, Fragrance, Sodium Benzoate, Glycol Distearate, Lauramide MIPA, Sodium Hydroxide, Disodium Cocamido MIPA Sulfosuccinate, D&C Geen 5, FD&C Yellow 5,

Usage

Anticacterial Hand Cleaner

Use in daycare, hospitals, nursing homes, physicians offices, dental offices, and clinics

instructions

Place enough product on your palm and scrub thoroughly over all surfaces of both hands

Rinse with clean water

active

Chloroxylenol

Keep ot of Reach

KEEP OUTOF REACH OF CHILDREN

If swallowed, get medical helo or contact Poison Control center right away

purpose

Antibacterial

Warnings

For external use only

when using this product avoid contact with eyes

If contact occurs, rinse thoroughly with water

Stop use and ask a doctor if irritation or rash occurs